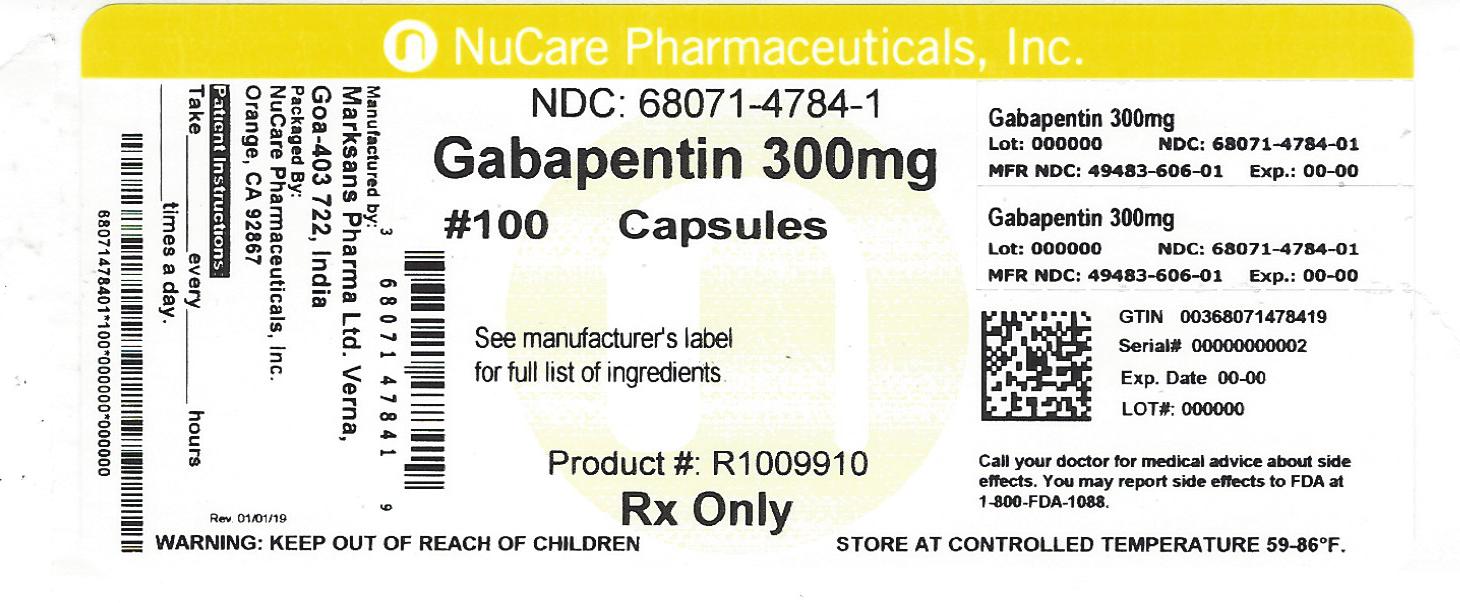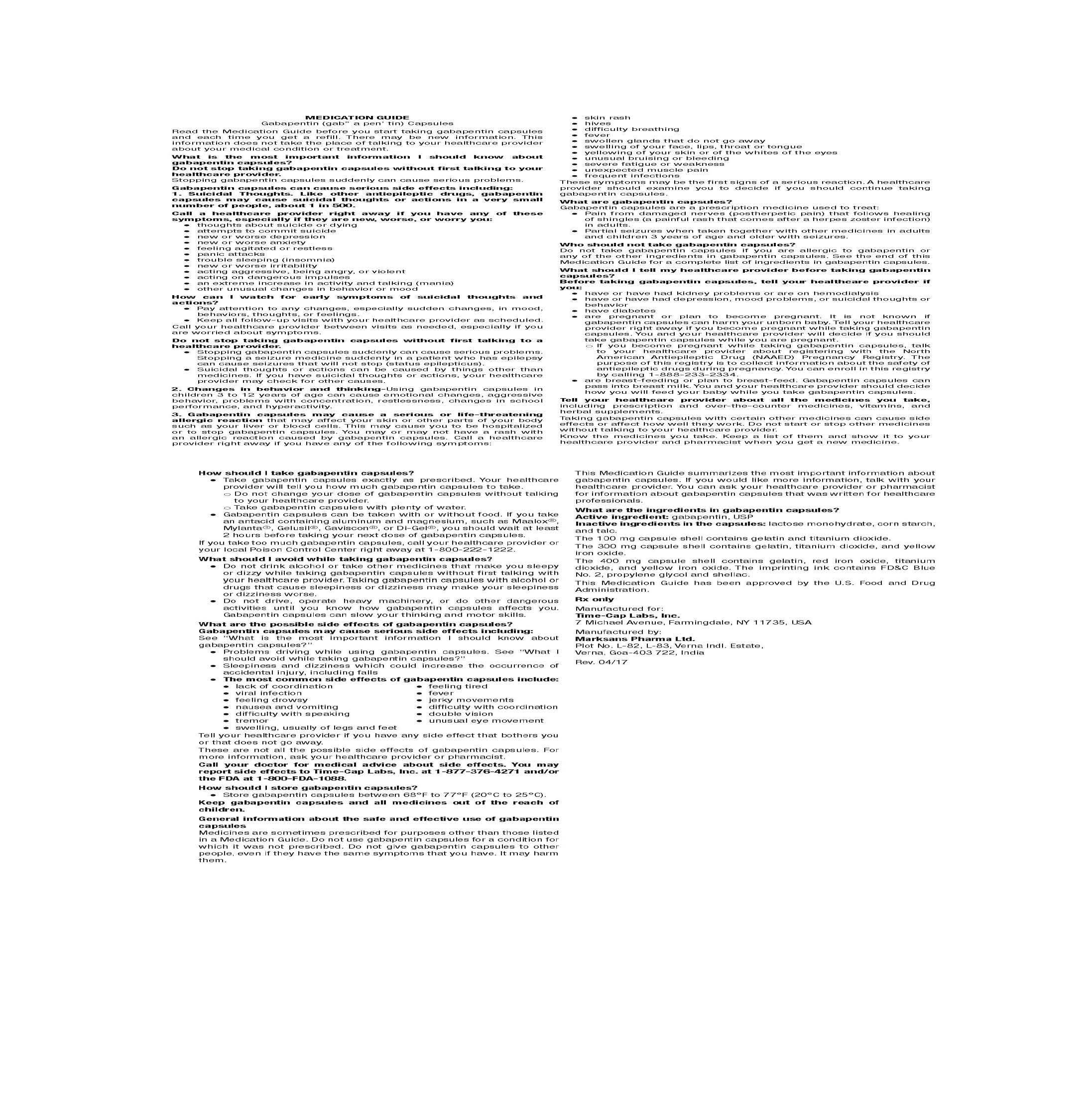 DRUG LABEL: GABAPENTIN
NDC: 68071-4784 | Form: CAPSULE
Manufacturer: NuCare Pharmaceuticals,Inc.
Category: prescription | Type: HUMAN PRESCRIPTION DRUG LABEL
Date: 20240614

ACTIVE INGREDIENTS: GABAPENTIN 300 mg/1 1
INACTIVE INGREDIENTS: LACTOSE MONOHYDRATE; STARCH, CORN; TALC; GELATIN; TITANIUM DIOXIDE; FERRIC OXIDE YELLOW; PROPYLENE GLYCOL; SHELLAC

HOW SUPPLIED

100 mg Capsules (White/White colored, size 3 hard gelatin capsules with 103 printed on body of capsules containing white to off white granular powder)

NDC 68071-4784-1 BOTTLES OF 100